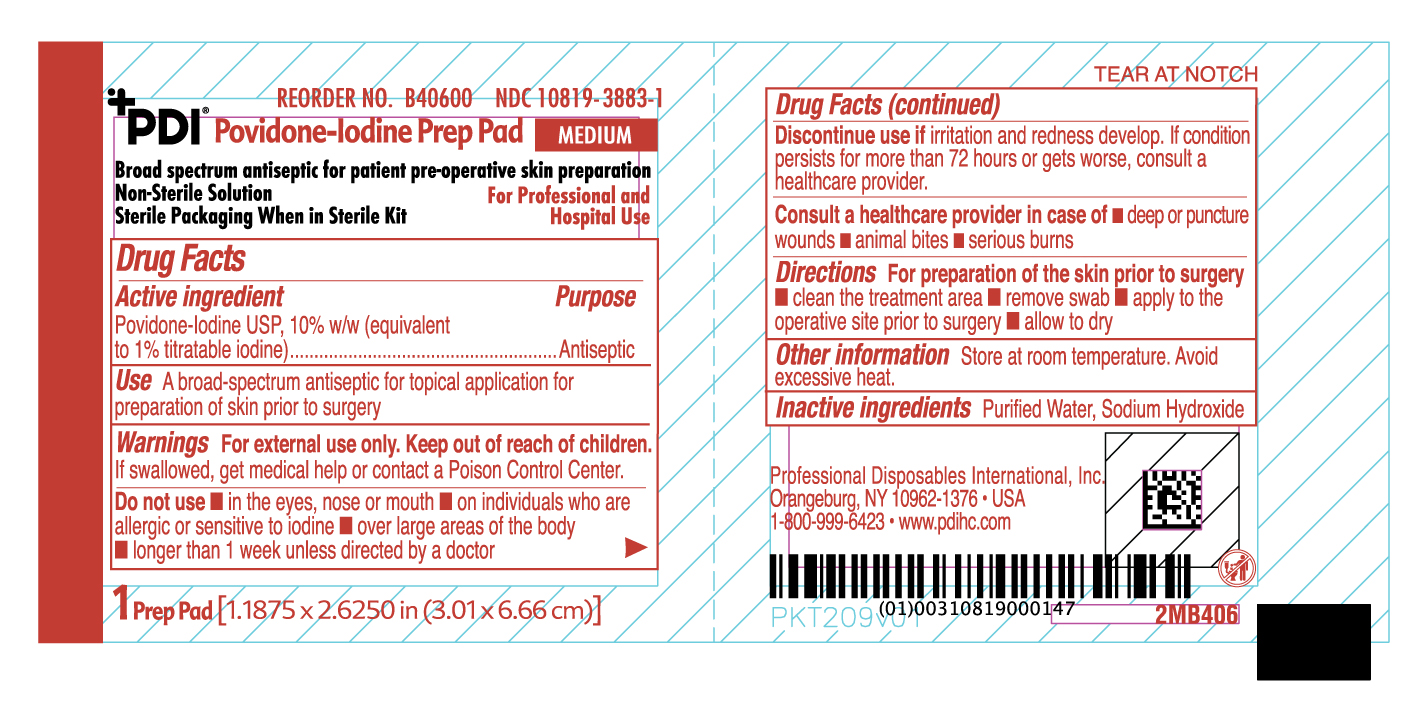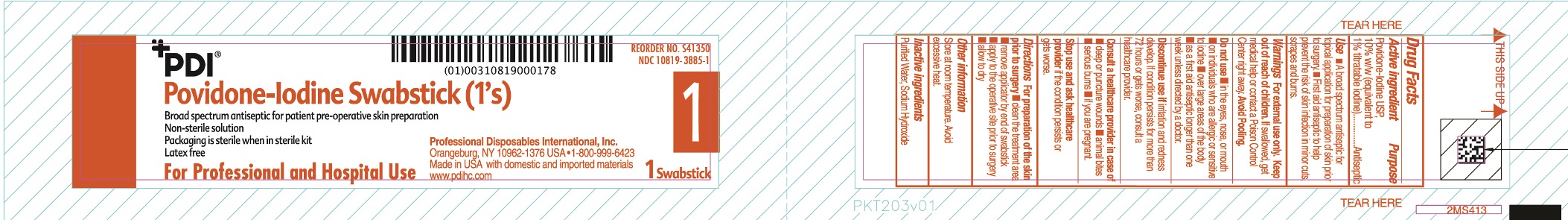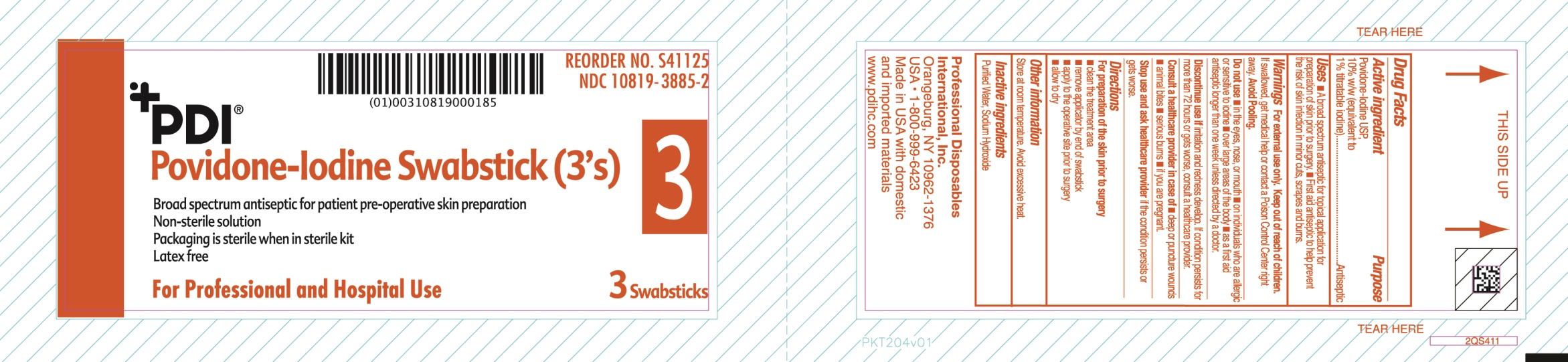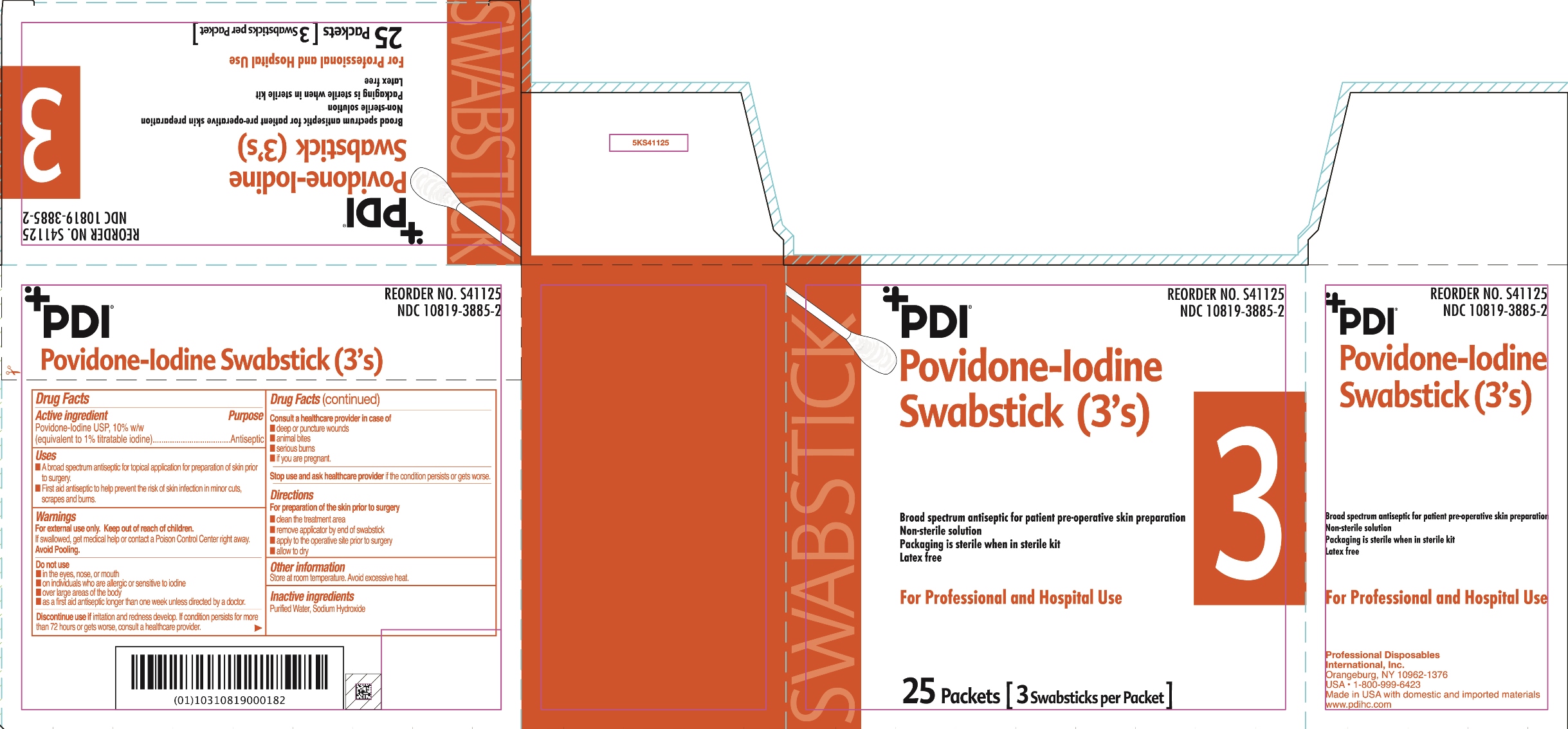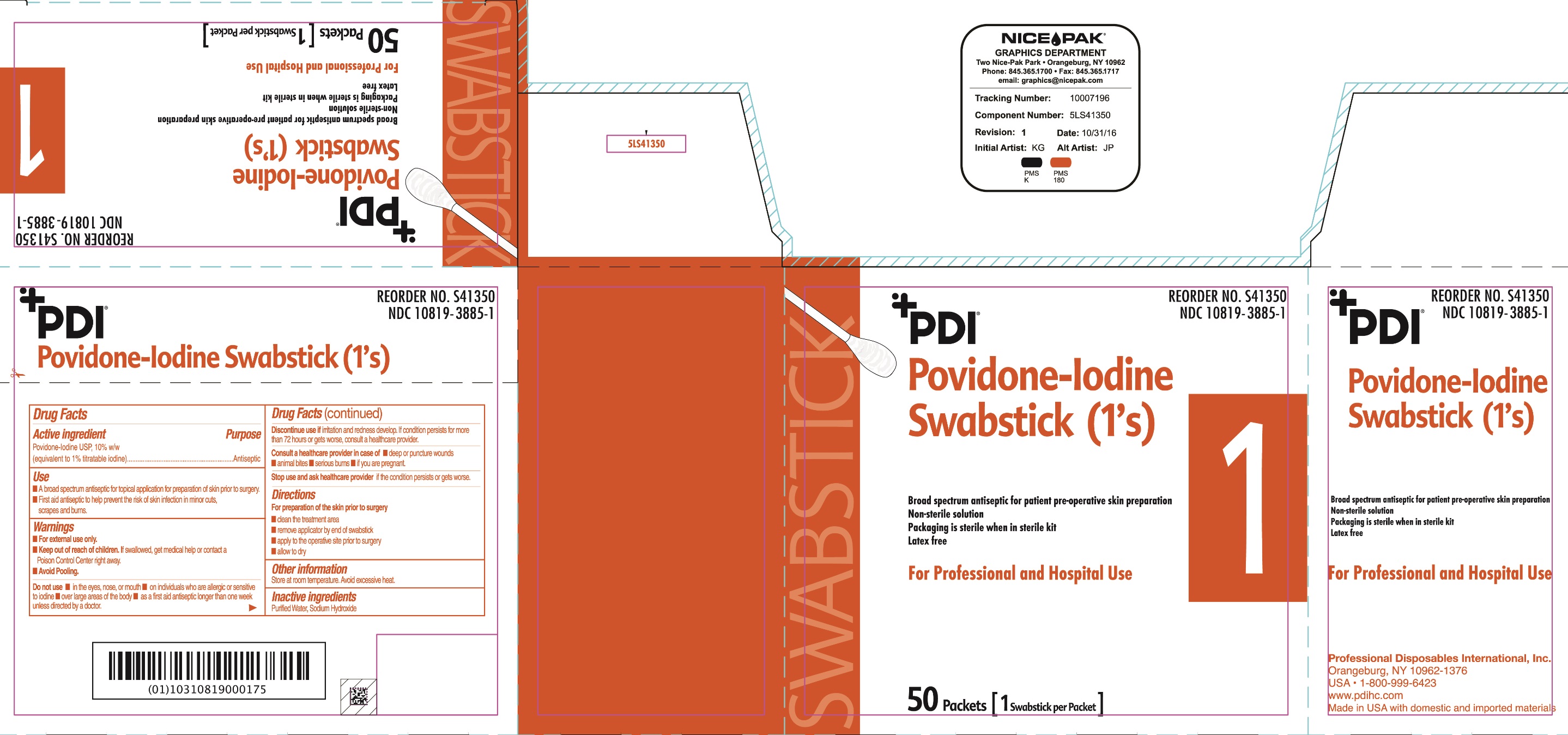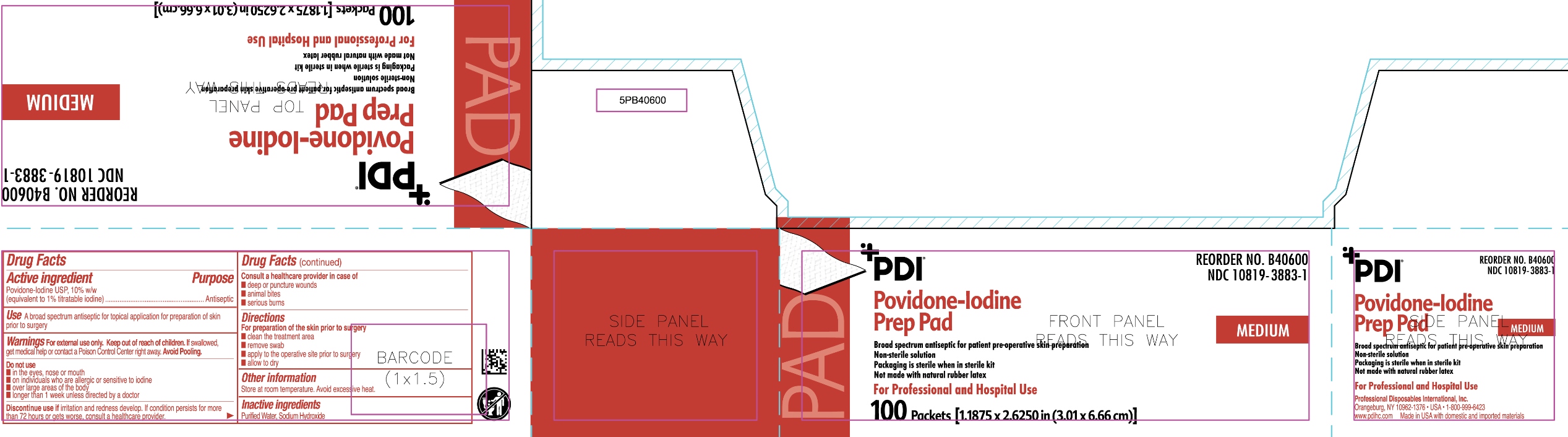 DRUG LABEL: PVP Iodine Prep Pad
NDC: 10819-3883 | Form: SWAB
Manufacturer: Professional Disposables International, Inc.
Category: otc | Type: HUMAN OTC DRUG LABEL
Date: 20251008

ACTIVE INGREDIENTS: POVIDONE-IODINE 10 mg/1 mL
INACTIVE INGREDIENTS: WATER; SODIUM HYDROXIDE

PVP-I

Active ingredient

Povidone-Iodine USP 10% w/w (equivalent to 1.0% titratable iodine)

Purpose

Antiseptic

Uses

- A broad spectrum antiseptic for topical application for preparation of the skin prior to surgery.

Warnings

For external use only

If swallowed, get medical help or contact a Poison Control Center.

Discontinue use if irritation and redness develop. If condition persist for more than 72 hours or gets worse, consult a healthcare provider

Directions

For preparation of the skin prior to surgery

- clean the treatment area
- remove swab
- apply to the operative site prior to surgery
- allow to dry

Other information

- Store at room temperature
- Avoid excessive heat

Inactive ingredients

Purified Water, Sodium Hydroxide

Do not use

- in the eyes, nose or mouth
- on individuals who are allergic or sensitive to iodine
- over large areas of the body
- longer than one week unless directed by a doctor

Consult a healthcare provider in case of

- deep or puncture wounds

- animal bites

- serious burns

Keep out of reach of children

Principal Display Panel

Packet 1 swabstick

Box 1 swabstick

Packet 3 swabsticks

Box 3 swabsticks

Packet med

Box med